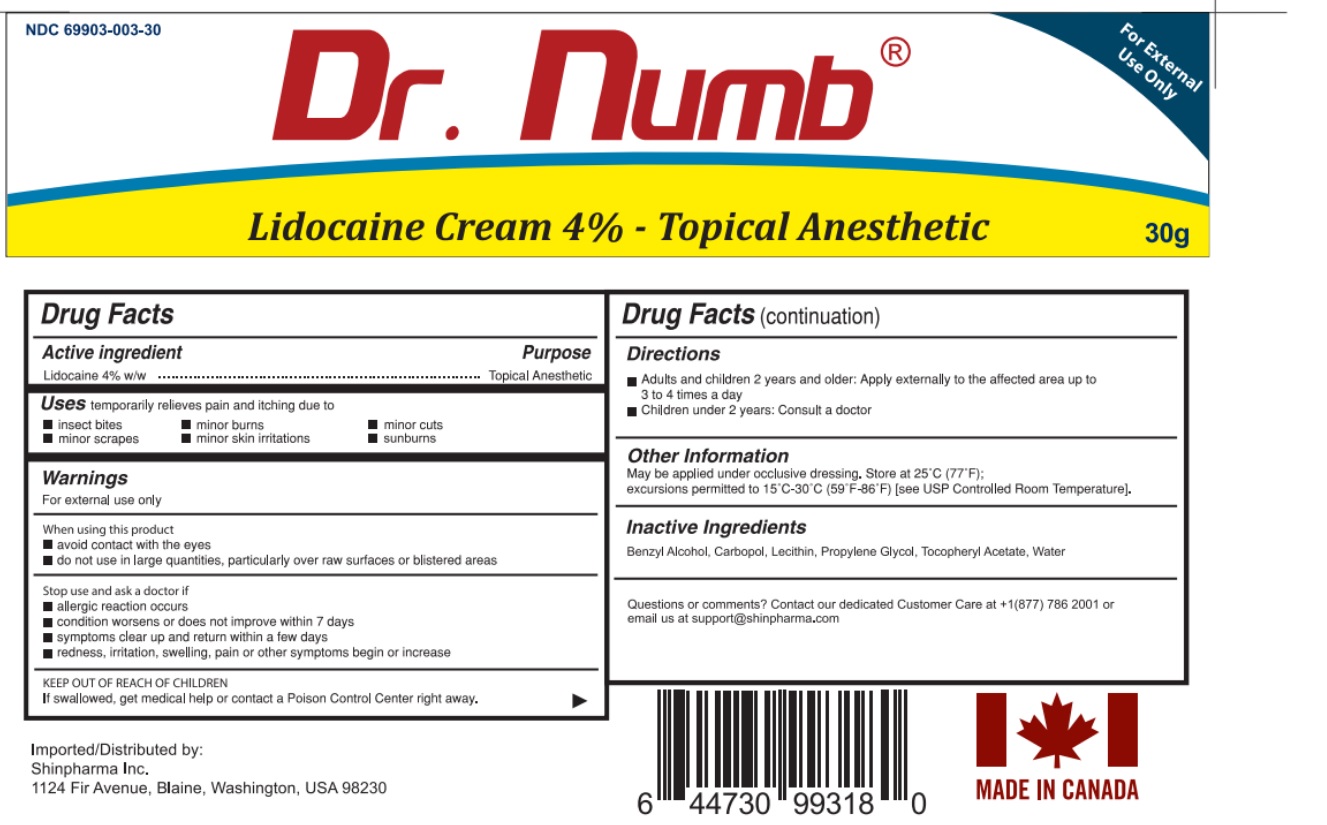 DRUG LABEL: Dr. Numb
NDC: 69903-003 | Form: CREAM
Manufacturer: Shinpharma Inc
Category: otc | Type: HUMAN OTC DRUG LABEL
Date: 20240403

ACTIVE INGREDIENTS: LIDOCAINE 1.2 g/30 g
INACTIVE INGREDIENTS: PROPYLENE GLYCOL BUTYL ETHER; TOCOPHERYL RETINOATE; WATER; BENZYL ALCOHOL; CARBOMER HOMOPOLYMER, UNSPECIFIED TYPE; LECITHIN, SOYBEAN

Drug Facts

Active ingredient

Lidocaine 4% w/w

Purpose

Topical Anesthetic

Uses

Temporarily relieves pain and itching due to

- insect bites
- minor burns
- minor cuts
- minor scrapes
- minor skin irritations
- sunburn

Warnings

For external use only

When using this product

- avoid contact with the eyes
- do not use in large quantities, particularly over raw surfaces or blistered areas

Stop the use and consult doctor if

- allergic reaction occurs
- condition worsens or does not improve within 7 days
- symptoms clear up and return within a few days
- redness, irritation, swelling, pain or other symptoms begin or increase

KEEP OUR OF REACH OF CHILDREN

If swallowed, get medical help or contact a Poison Control Center right away

Directions

- Adults and children 2 years and older: Apply externally to the affected area up to 3 to 4 times a day
- Children under 2 years: Consult a doctor

Other Information

- May be applied under occlusive dressing.
- Store at 25 ̊C (77 ̊F);
- excursions permitted to 15°C -30°C (59°F - 86°F) [see USP Controlled Room Temperature].

Inactive Ingredients

Benzyl Alcohol, Carbopol, Lecithin(Soybean), Propylene Glycol, Tocopheryl Acetate, Water.

Question or Comments

Contact our dedicated Customer Care at +1(877) 786 2001 or email us at support@shinpharma.com

Principal Display Panel

NDC 69903-003-30

Water-based, Hypoallergenic and Fast Penetrating Topical Pain Relief and Anti-Itch Formula

Apply to the skin to relieve pain

FOR EXTERNAL USE ONLY

Dr. Numb

TOPICAL ANESTHETIC CREAM

Lidocaine 4% Cream - Topical Anesthetic

30g